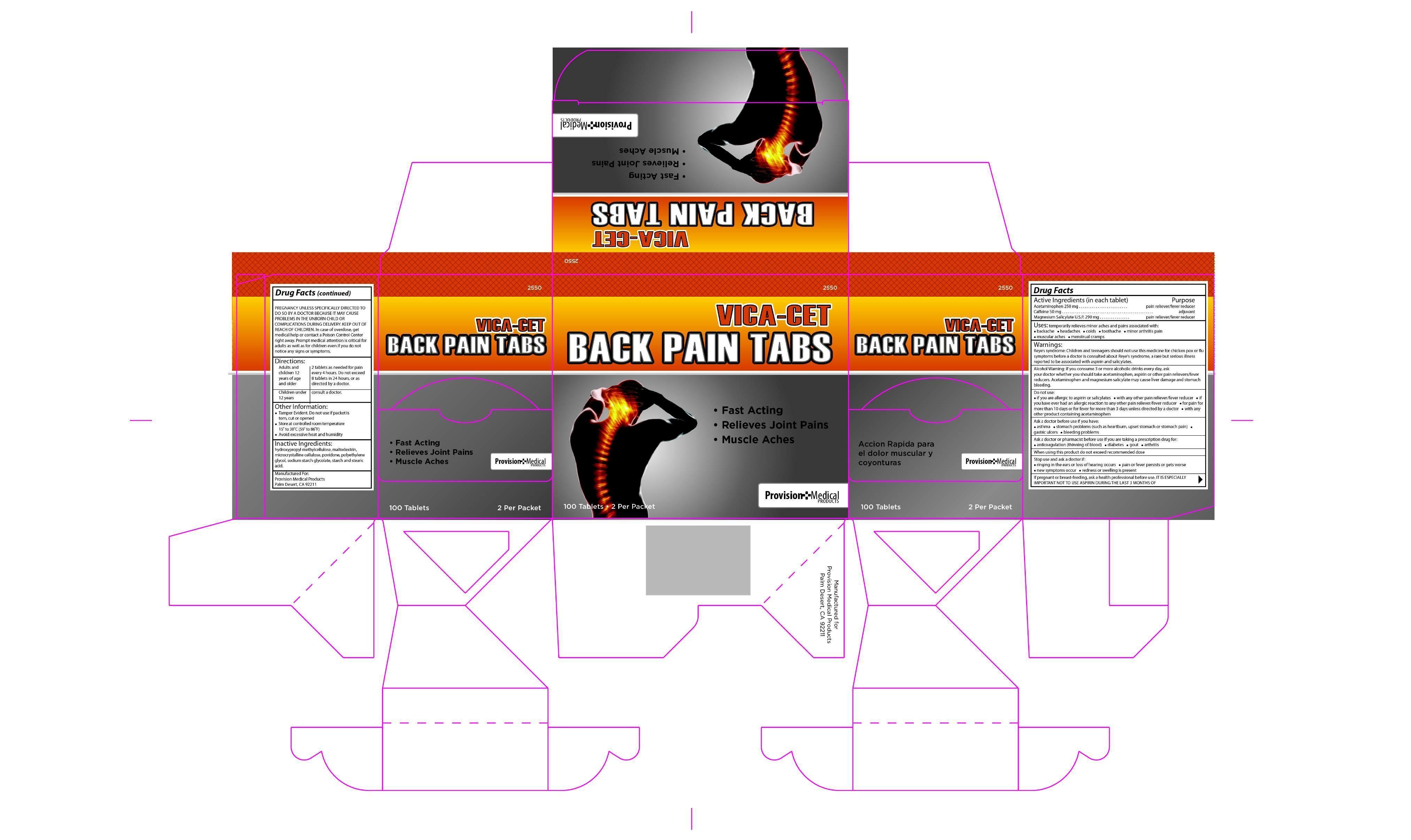 DRUG LABEL: VICA-CET
NDC: 69103-2550 | Form: TABLET
Manufacturer: Provision Medical Products
Category: otc | Type: HUMAN OTC DRUG LABEL
Date: 20150405

ACTIVE INGREDIENTS: MAGNESIUM SALICYLATE 250 mg/1 1; ACETAMINOPHEN 250 mg/1 1
INACTIVE INGREDIENTS: CAFFEINE; STEARIC ACID; CELLULOSE, MICROCRYSTALLINE; POVIDONE K30; STARCH, PREGELATINIZED CORN; TITANIUM DIOXIDE; HYPROMELLOSES; MALTODEXTRIN; POLYETHYLENE GLYCOL 400

Uses:

for temporary relief of mild to moderate pain

associated with BACKACHE, headache, colds. toothache, minor arthritis pain, muscular aches, menstrual cramps

If pregnant or breast-feeding, ask a

health professional before use. IT IS

ESPECIALLY IMPORTANT NOT TO USE

DURING THE LAST 3 MONTHS

OF PREGNANCY UNLESS SPECIFICALLY

DIRECTED TO DO SO BY A DOCTOR,

BECAUSE IT MAY CAUSE PROBLEMS IN

THE UNBORN CHILD OR

COMPLICATIONS DURING DELIVERY.

KEEP OUT OF REACH OF CHILDREN. In

case of overdose, get medical help or

contact a Poison Control Center right

away. Prompt medical attention is

critical for adults as well as for children

even if you do not notice any signs or

symptoms.

Warnings:

Reye's syndrome: Children and teenagers should not

use this medicine for chicken pox or 　u symptoms

before a doctor is consulted about Reye's syndrome, a

rare but serious illness reported to be associated with

aspirin.

Allergy Alert: Do not take this product if after

taking a pain reliever or fever reducer you ever had • hives • facial swelling • asthma • shock

Alcohol Warning: If you consume 3 or more

alcoholic drinks every day, ask your doctor whether you

should take acetaminophen and aspirin or other pain

relievers/fever reducers. Acetaminophen and aspirin may

cause liver damage and stomach bleeding.

Ask a doctor before use if you have: • the worst headache of your life • ulcers

• fever and sti neck • asthma

• bleeding problems • liver disease

• renal disease

When using this product:

• limit the use of caffeine containing medications,

foods, or beverages while taking this product

because too much caFFeine may cause

nervousness, sleeplessness, irritability and,

occasionally, rapid heart beat.

Stop use and ask a doctor if:

• headache pain worsens or continues for more than 48 hours

• new or unexpected symptoms occur

• ringing in the ears or loss of hearing occur

Directions:

Adults and children 12 years of age, no to exceed 8 tablets in 24 hours, or as directed by a doctor.

Children under 12 years: Do not give to children under 12 unless directed by a doctor.

Inactive Ingredients:

hydroxypropyl methylcellulose, maltodextrin,microcrystalline cellulose,polyethylene glycol

povidone, sodium starch glycolate, starch, and stearic acid

USP.

ACTIVE INGREDIENT-ACETAMINOPHEN 250 MG, MAGNESIUM SALICYLAYE 250 MG,CAFFEINE 50 mg

PURPOSE

PAIN RELIEVER, FEVER REDUCER WITH ADJUVANT